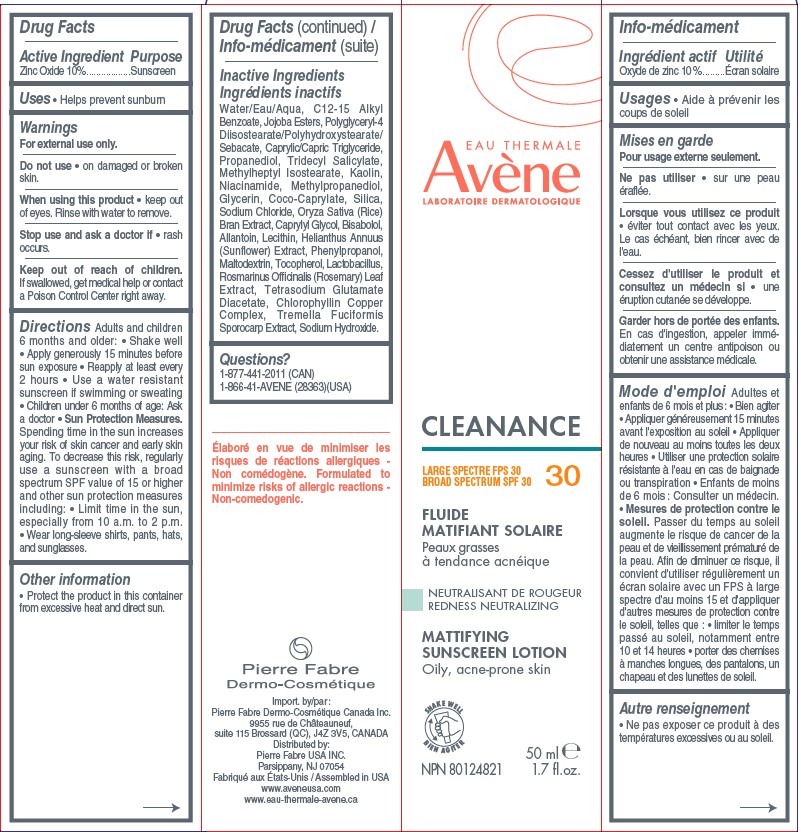 DRUG LABEL: Avene Cleanance Mattifying SPF 30
NDC: 64760-786 | Form: LOTION
Manufacturer: Pierre Fabre USA Inc.
Category: otc | Type: HUMAN OTC DRUG LABEL
Date: 20241106

ACTIVE INGREDIENTS: ZINC OXIDE 100 mg/1 mL
INACTIVE INGREDIENTS: WATER; ALKYL (C12-15) BENZOATE; POLYGLYCERYL-4 DIISOSTEARATE/POLYHYDROXYSTEARATE/SEBACATE; RICE BRAN; BIFIDOBACTERIUM ANIMALIS LACTIS; TREMELLA FUCIFORMIS FRUITING BODY; ALLANTOIN; TETRASODIUM GLUTAMATE DIACETATE; PROPANEDIOL; TRIDECYL SALICYLATE; METHYLPROPANEDIOL; SODIUM CHLORIDE; SODIUM HYDROXIDE; METHYLHEPTYL ISOSTEARATE; JOJOBA OIL, RANDOMIZED; NIACINAMIDE; COCO-CAPRYLATE; MEDIUM-CHAIN TRIGLYCERIDES; KAOLIN; GLYCERIN; SILICON DIOXIDE; CAPRYLYL GLYCOL; LEVOMENOL; LECITHIN, SOYBEAN; MALTODEXTRIN; TOCOPHEROL; ROSEMARY; SODIUM COPPER CHLOROPHYLLIN; HELIANTHUS ANNUUS FLOWERING TOP; PHENYLPROPANOL

Avene Cleanance Mattifying Lotion SPF 30

Active ingredient

Zinc oxide 10%

Purpose

Sunscreen

Uses

• Helps prevent sunburn

Warnings

For external use only.

Do not use

• on damaged or broken skin.

When using this product

• keep out of eyes. Rinse with water to remove.

Stop use and ask a doctor if •

• rash occurs.

Keep out of reach of children.

If swallowed, call a poison control center or get medical help right away.

Directions

Adults and children 6 months and older:

• Shake well • Apply generously 15 minutes before sun exposure • Reapply at least every 2 hours • Use a water resistant sunscreen if swimming or sweating • Children under 6 months of age: Ask a doctor • Sun Protection Measures. Spending time in the sun increases your risk of skin cancer and early skin aging. To decrease this risk, regularly use a sunscreen with a broad spectrum SPF value of 15 or higher and other sun protection measures including: • Limit time in the sun, especially from 10 a.m. to 2 p.m. • Wear long-sleeve shirts, pants, hats, and sunglasses.

Other information

• Protect the product in this container from excessive heat and direct sun.

Inactive Ingredients

Water/Eau/Aqua, C12-15 Alkyl Benzoate, Jojoba Esters, Polyglyceryl-4 Diisostearate/Polyhydroxystearate/Sebacate, Caprylic/Capric Triglyceride, Propanediol, Tridecyl Salicylate, Methylheptyl Isostearate, Kaolin, Niacinamide, Methylpropanediol, Glycerin, Coco-Caprylate, Silica, Sodium Chloride, Oryza Sativa (Rice) Bran Extract, Caprylyl Glycol, Bisabolol, Allantoin, Lecithin, Helianthus Annuus
(Sunflower) Extract, Phenylpropanol, Maltodextrin, Tocopherol, Lactobacillus, Rosmarinus Officinalis (Rosemary) Leaf Extract, Tetrasodium Glutamate Diacetate, Chlorophyllin Copper Complex, Tremella Fuciformis Sporocarp Extract, Sodium Hydroxide.

Questions?

1-877-441-2011 (CAN)
1-866-41-AVENE (28363)(USA)